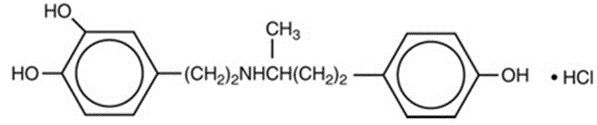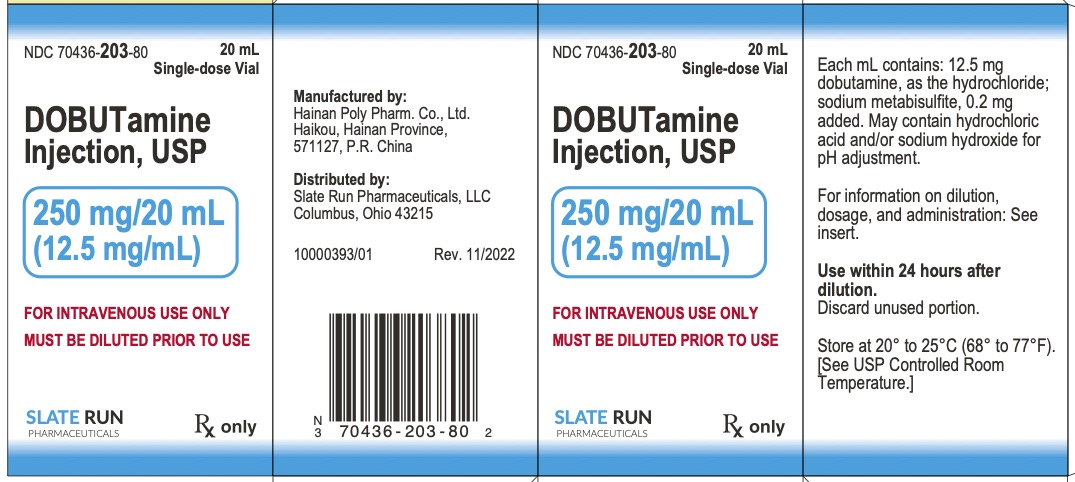 DRUG LABEL: Dobutamine
NDC: 70436-203 | Form: INJECTION
Manufacturer: Slate Run Pharmaceuticals
Category: prescription | Type: HUMAN PRESCRIPTION DRUG LABEL
Date: 20260126

ACTIVE INGREDIENTS: DOBUTAMINE HYDROCHLORIDE 250 mg/20 mL
INACTIVE INGREDIENTS: SODIUM METABISULFITE; HYDROCHLORIC ACID; SODIUM HYDROXIDE

Dobutamine injection

DESCRIPTION

Dobutamine Injection, USP is a clear, practically colorless, sterile, nonpyrogenic solution of dobutamine hydrochloride for intravenous use only. Each milliliter contains 12.5 mg (41.5 µmol) dobutamine, as the hydrochloride and sodium metabisulfite, 0.2 mg added as antioxidant. May contain hydrochloric acid and/or sodium hydroxide for pH adjustment. pH is 3.3 (2.5 to 5.0).

Dobutamine Hydrochloride, USP is chemically designated (±)-4-[2-[[3-(ρ-hydroxyphenyl)-1- methylpropyl] amino]ethyl]-pyrocatechol hydrochloride.

It is a synthetic catecholamine.

Molecular Weight: 337.85

Molecular Formula: C18H23NO3• HCl

CLINICAL PHARMACOLOGY

Dobutamine is a direct-acting inotropic agent whose primary activity results from stimulation of the β receptors of the heart while producing comparatively mild chronotropic, hypertensive, arrhythmogenic, and vasodilative effects. It does not cause the release of endogenous norepinephrine, as does dopamine. In animal studies, dobutamine produces less increase in heart rate and less decrease in peripheral vascular resistance for a given inotropic effect than does isoproterenol.

In patients with depressed cardiac function, both dobutamine and isoproterenol increase the cardiac output to a similar degree. In the case of dobutamine, this increase is usually not accompanied by marked increases in heart rate (although tachycardia is occasionally observed), and the cardiac stroke volume is usually increased. In contrast, isoproterenol increases the cardiac index primarily by increasing the heart rate while stroke volume changes little or declines.

Facilitation of atrioventricular conduction has been observed in human electrophysiologic studies and in patients with atrial fibrillation.

Systemic vascular resistance is usually decreased with administration of dobutamine. Occasionally, minimum vasoconstriction has been observed.

Most clinical experience with dobutamine is short-term − not more than several hours in duration. In the limited number of patients who were studied for 24, 48, and 72 hours, a persistent increase in cardiac output occurred in some, whereas output returned toward baseline values in others.

The onset of action of dobutamine is within 1 to 2 minutes; however, as much as 10 minutes may be required to obtain the peak effect of a particular infusion rate.

The plasma half-life of dobutamine in humans is 2 minutes. The principal routes of metabolism are methylation of the catechol and conjugation. In human urine, the major excretion products are the conjugates of dobutamine and 3-O-methyl dobutamine. The 3-O-methyl derivative of dobutamine is inactive.

Alteration of synaptic concentrations of catecholamines with either reserpine or tricyclic antidepressants does not alter the actions of dobutamine in animals, which indicates that the actions of dobutamine are not dependent on presynaptic mechanisms.

The effective infusion rate of dobutamine varies widely from patient to patient, and titration is always necessary (see Dosage and Administration). At least in pediatric patients, dobutamine-induced increases in cardiac output and systemic pressure are generally seen, in any given patients, at lower infusion rates than those that cause substantial tachycardia (see Pediatric Useunder Precautions).

INDICATIONS AND USAGE

Dobutamine Injection, USP is indicated when parenteral therapy is necessary for inotropic support in the short-term treatment of patients with cardiac decompensation due to depressed contractility resulting either from organic heart disease or from cardiac surgical procedures. Experience with intravenous dobutamine in controlled trials does not extend beyond 48 hours of repeated boluses and/or continuous infusions.

Whether given orally, continuously intravenously, or intermittently intravenously, neither dobutamine nor any other cyclic-AMP-dependent inotrope has been shown in controlled trials to be safe or effective in the long-term treatment of congestive heart failure. In controlled trials of chronic oral therapy with various such agents, symptoms were not consistently alleviated, and the cyclic-AMP-dependent inotropes were consistently associated with increased risk of hospitalization and death. Patients with NYHA Class IV symptoms appeared to be at particular risk.

CONTRAINDICATIONS

Dobutamine hydrochloride is contraindicated in patients with idiopathic hypertrophic subaortic stenosis and in patients who have shown previous manifestations of hypersensitivity to Dobutamine Injection solution.

WARNINGS

1. Increase in Heart Rate or Blood Pressure
2. Dobutamine hydrochloride may cause a marked increase in heart rate or blood pressure, especially systolic pressure. Approximately 10% of patients in clinical studies have had rate increases of 30 beats/minute or more, and about 7.5% have had a 50 mm Hg or greater increase in systolic pressure. Usually, reduction of dosage promptly reverses these effects. Because dobutamine hydrochloride facilitates atrioventricular conduction, patients with atrial fibrillation are at risk of developing rapid ventricular response. In patients who have atrial fibrillation with rapid ventricular response, a digitalis preparation should be used prior to institution of therapy with Dobutamine Injection. Patients with pre-existing hypertension appear to face an increased risk of developing an exaggerated pressor response.
3. Ectopic Activity
4. Dobutamine hydrochloride may precipitate or exacerbate ventricular ectopic activity, but it rarely has caused ventricular tachycardia.
5. Hypersensitivity
6. Reactions suggestive of hypersensitivity associated with administration of Dobutamine Injection, including skin rash, fever, eosinophilia, and bronchospasm, have been reported occasionally. Dobutamine Injection contains sodium metabisulfite, a sulfite that may cause allergic-type reactions, including anaphylactic symptoms and life-threatening or less severe asthmatic episodes, in certain susceptible people. The overall prevalence of sulfite sensitivity in the general population is unknown and probably low. Sulfite sensitivity is seen more frequently in asthmatic than in nonasthmatic people.

PRECAUTIONS

General

1. During the administration of Dobutamine Injection, as with any adrenergic agent, ECG and blood pressure should be continuously monitored. In addition, pulmonary wedge pressure and cardiac output should be monitored whenever possible to aid in the safe and effective infusion of dobutamine hydrochloride.
2. Hypovolemia should be corrected with suitable volume expanders before treatment with dobutamine hydrochloride is instituted.
3. No improvement may be observed in the presence of marked mechanical obstruction, such as severe valvular aortic stenosis.

Usage Following Acute Myocardial Infarction

Clinical experience with dobutamine hydrochloride following myocardial infarction has been insufficient to establish the safety of the drug for this use. There is concern that any agent that increases contractile force and heart rate may increase the size of an infarction by intensifying ischemia, but it is not known whether dobutamine hydrochloride does so.

Laboratory Tests

Dobutamine, like other β2-agonists, can produce a mild reduction in serum potassium concentration, rarely to hypokalemic levels. Accordingly, consideration should be given to monitoring serum potassium.

Drug Interactions

Animal studies indicate that dobutamine may be ineffective if the patient has recently received a β-blocking drug. In such a case, the peripheral vascular resistance may increase.

Preliminary studies indicate that the concomitant use of dobutamine and nitroprusside results in a higher cardiac output and, usually, a lower pulmonary wedge pressure than when either drug is used alone.

There was no evidence of drug interactions in clinical studies in which dobutamine was administered concurrently with other drugs, including digitalis preparations, furosemide, spironolactone, lidocaine, nitroglycerin, isosorbide dinitrate, morphine, atropine, heparin, protamine, potassium chloride, folic acid, and acetaminophen.

Carcinogenesis, Mutagenesis, Impairment of Fertility

Studies to evaluate the carcinogenic or mutagenic potential of dobutamine hydrochloride, or its potential to affect fertility, have not been conducted.

Pregnancy

Teratogenic Effects−Reproduction studies performed in rats at doses up to the normal human dose (10 mcg/kg/min for 24 h, total daily dose of 14.4 mg/kg), and in rabbits at doses up to twice the normal human dose, have revealed no evidence of harm to the fetus due to dobutamine hydrochloride. There are, however, no adequate and well-controlled studies in pregnant women. Because animal reproduction studies are not always predictive of human response, this drug should be used during pregnancy only if clearly needed.

Labor and Delivery

The effect of dobutamine hydrochloride on labor and delivery is unknown.

Nursing Mothers

It is not known whether this drug is excreted in human milk. Because many drugs are excreted in human milk, caution should be exercised when dobutamine hydrochloride is administered to a nursing woman. If a mother requires dobutamine hydrochloride treatment, breastfeeding should be discontinued for the duration of treatment.

Pediatric Use

Dobutamine has been shown to increase cardiac output and systemic pressure in pediatric patients of every age group. In premature neonates, however, dobutamine is less effective than dopamine in raising systemic blood pressure without causing undue tachycardia, and dobutamine has not been shown to provide any added benefit when given to such infants already receiving optimal infusion of dopamine.

Geriatric Use

Of the 1893 patients in clinical studies who were treated with dobutamine, 930 (49.1%) were 65 and older. No overall differences in safety or effectiveness were observed between these and younger subjects. Other reported clinical experience has not identified differences in responses between the elderly and younger patients, but greater sensitivity of some older individuals cannot be ruled out.

In general, dose selection for an elderly patient should be cautious, usually starting at the low end of the dosing range, reflecting the greater frequency of decreased hepatic, renal, or cardiac function, and of concomitant disease or drug therapy.

ADVERSE REACTIONS

Increased Heart Rate, Blood Pressure, and Ventricular Ectopic Activity −A 10 to 20 mm increase in systolic blood pressure and an increase in heart rate of 5 to 15 beats/minute have been noted in most patients (see WARNINGSregarding exaggerated chronotropic and pressor effects). Approximately 5% of patients have had increased premature ventricular beats during infusions. These effects are dose related.

Hypotension− Precipitous decreases in blood pressure have occasionally been described in association with dobutamine therapy. Decreasing the dose or discontinuing the infusion typically results in rapid return of blood pressure to baseline values. In rare cases, however, intervention may be required and reversibility may not be immediate.

Reactions at Sites of Intravenous Infusion− Phlebitis has occasionally been reported. Local inflammatory changes have been described following inadvertent infiltration. Isolated cases of cutaneous necrosis (destruction of skin tissue) have been reported.

Miscellaneous Uncommon Effects− The following adverse effects have been reported in 1% to 3% of patients: nausea, headache, anginal pain, nonspecific chest pain, palpitations and shortness of breath. Isolated cases of thrombocytopenia have been reported.

Administration of dobutamine hydrochloride, like other catecholamines, can produce a mild reduction in serum potassium concentration, rarely to hypokalemic levels (see PRECAUTIONS).

OVERDOSAGE

Overdoses of dobutamine have been reported rarely. The following is provided to serve as a guide if such an overdose is encountered.

Signs and Symptoms− Toxicity from dobutamine is usually due to excessive cardiac β-receptor stimulation. The duration of action of dobutamine is generally short (T1/2= 2 minutes) because it is rapidly metabolized by catechol-O-methyltransferase. The symptoms of toxicity may include anorexia, nausea, vomiting, tremor, anxiety, palpitations, headache, shortness of breath, and anginal and nonspecific chest pain. The positive inotropic and chronotropic effects of dobutamine on the myocardium may cause hypertension, tachyarrhythmias, myocardial ischemia, and ventricular fibrillation. Hypotension may result from vasodilation.

Treatment− To obtain up-to-date information about the treatment of overdose, a good resource is your certified Regional Poison Control Center. Telephone numbers of certified poison control centers are listed in the Physicians' Desk Reference (PDR). In managing overdosage, consider the possibility of multiple drug overdoses, interaction among drugs, and unusual drug kinetics in your patient.

The initial actions to be taken in a dobutamine overdose are discontinuing administration, establishing an airway, and ensuring oxygenation and ventilation. Resuscitative measures should be initiated promptly. Severe ventricular tachyarrhythmias may be successfully treated with propranolol or lidocaine. Hypertension usually responds to a reduction in dose or discontinuation of therapy.

Protect the patient's airway and support ventilation and perfusion. If needed, meticulously monitor and maintain, within acceptable limits, the patient's vital signs, blood gases, serum electrolytes, etc. If the product is ingested, unpredictable absorption may occur from the mouth and the gastrointestinal tract. Absorption of drugs from the gastrointestinal tract may be decreased by giving activated charcoal, which, in many cases, is more effective than emesis or lavage; consider charcoal instead of or in addition to gastric emptying. Repeated doses of charcoal over time may hasten elimination of some drugs that have been absorbed. Safeguard the patient's airway when employing gastric emptying or charcoal.

Forced diuresis, peritoneal dialysis, hemodialysis, or charcoal hemo-perfusion have not been established as beneficial for an overdose of dobutamine.

DOSAGE AND ADMINISTRATION

Note−Do not add dobutamine injection to 5% Sodium Bicarbonate Injection or to any other strongly alkaline solution. Because of potential physical incompatibilities, it is recommended that dobutamine injection not be mixed with other drugs in the same solution. Dobutamine injection should not be used in conjunction with other agents or diluents containing both sodium bisulfite and ethanol.

Preparation and Stability− At the time of administration, dobutamine injection must be further diluted in an IV container to at least a 50-mL solution using one of the following intravenous solutions as a diluent: 5% Dextrose Injection, 5% Dextrose and 0.45% Sodium Chloride Injection, 5% Dextrose and 0.9% Sodium Chloride Injection, 10% Dextrose Injection, Isolyte® M with 5% Dextrose Injection, Lactated Ringer’s Injection, 5% Dextrose in Lactated Ringer’s Injection, Normosol®-M in D5-W, 20% Osmitrol® in Water for Injection, 0.9% Sodium Chloride Injection, or Sodium Lactate Injection. Intravenous solution should be used within 24 hours.

Recommended Dosage−Infusion of dobutamine should be started at a low rate (0.5-1.0 μg/kg/min) and titrated at intervals of a few minutes, guided by the patient’s response, including systemic blood pressure, urine flow, frequency of ectopic activity, heart rate, and (whenever possible) measurements of cardiac output, central venous pressure, and/or pulmonary capillary wedge pressure. In reported trials, the optimal infusion rates have varied from patient to patient, usually 2-20 μg/kg/min but sometimes slightly outside of this range. On rare occasions, infusion rates up to 40 μg/kg/min have been required to obtain the desired effect. Rates of infusion (mL/h) for dobutamine injection concentrations of 500 μg/mL, 1,000 μg/mL, and 2,000 μg/mL necessary to attain various delivery rates of dobutamine (μg/kg/min) for patients of different weights are given in Table 1.

Table 1 Dobutamine Injection Infusion Rate (mL/h) for 500 μg/mL concentration

Drug Delivery Rate (μg/kg/min) | Patient Body Weight (kg)
Drug Delivery Rate (μg/kg/min) | 5 | 10 | 20 | 30 | 40 | 50 | 60 | 70 | 80 | 90 | 100 | 110
0.5 | 0.3 | 0.6 | 1.2 | 1.8 | 2.4 | 3 | 3.6 | 4.2 | 4.8 | 5.4 | 6 | 6.5
1 | 0.6 | 1.2 | 2.4 | 3.6 | 4.8 | 6 | 7.2 | 8.4 | 9.6 | 10.8 | 12 | 13.2
2.5 | 1.5 | 3 | 6 | 9 | 12 | 15 | 18 | 21 | 24 | 27 | 30 | 33
5 | 3 | 6 | 12 | 18 | 24 | 30 | 36 | 42 | 48 | 54 | 60 | 66
7.5 | 4.5 | 9 | 18 | 27 | 36 | 45 | 54 | 63 | 72 | 81 | 90 | 99
10 | 6 | 12 | 24 | 36 | 48 | 60 | 72 | 84 | 96 | 108 | 120 | 132
12.5 | 7.5 | 15 | 30 | 45 | 60 | 75 | 90 | 105 | 120 | 135 | 150 | 165
15 | 9 | 18 | 36 | 54 | 72 | 90 | 108 | 126 | 144 | 162 | 180 | 198
17.5 | 10.5 | 21 | 42 | 63 | 84 | 105 | 126 | 147 | 168 | 189 | 210 | 231
20 | 12 | 24 | 48 | 72 | 96 | 120 | 144 | 168 | 192 | 216 | 240 | 264

Dobutamine Injection Infusion Rate (mL/h) for 1,000 μg/mL concentration

Drug Delivery Rate (μg/kg/min) | Patient Body Weight (kg)
Drug Delivery Rate (μg/kg/min) | 5 | 10 | 20 | 30 | 40 | 50 | 60 | 70 | 80 | 90 | 100 | 110
0.5 | 0.1 | 0.3 | 0.6 | 0.9 | 1.2 | 1.5 | 1.8 | 2.1 | 2.4 | 2.7 | 3 | 3.3
1 | 0.3 | 0.6 | 1.2 | 1.8 | 2.4 | 3 | 3.6 | 4.2 | 4.8 | 5.4 | 6 | 6.6
2.5 | 0.7 | 1.5 | 3 | 4.5 | 6 | 7.5 | 9 | 10.5 | 12 | 13.5 | 15 | 16.5
5 | 1.5 | 3 | 6 | 9 | 12 | 15 | 18 | 21 | 24 | 27 | 30 | 33
7.5 | 2.2 | 4.5 | 9 | 13.5 | 18 | 22.5 | 27 | 31.5 | 36 | 40.5 | 45 | 49.5
10 | 3 | 6 | 12 | 18 | 24 | 30 | 36 | 42 | 48 | 54 | 60 | 66
12.5 | 3.7 | 7.5 | 15 | 22.5 | 30 | 37.5 | 45 | 52.5 | 60 | 67.5 | 75 | 82.5
15 | 4.5 | 9 | 18 | 27 | 36 | 45 | 54 | 63 | 72 | 81 | 90 | 99
17.5 | 5.2 | 10.5 | 21 | 31.5 | 42 | 52.5 | 63 | 73.5 | 84 | 94.5 | 105 | 115.5
20 | 6 | 12 | 24 | 36 | 48 | 60 | 72 | 84 | 96 | 108 | 120 | 132

Dobutamine Injection Infusion Rate (mL/h) for 2,000 μg/mL concentration

Drug Delivery Rate (μg/kg/min) | Patient Body Weight (kg)
Drug Delivery Rate (μg/kg/min) | 5 | 10 | 20 | 30 | 40 | 50 | 60 | 70 | 80 | 90 | 100 | 110
0.5 | 0.07 | 0.1 | 0.3 | 0.4 | 0.6 | 0.7 | 0.9 | 1 | 1.2 | 1.3 | 1.5 | 1.6
1 | 0.1 | 0.3 | 0.6 | 0.9 | 1.2 | 1.5 | 1.8 | 2.1 | 2.4 | 2.7 | 3 | 3.3
2.5 | 0.4 | 0.7 | 1.5 | 2 | 3 | 4 | 4.5 | 5 | 6 | 7 | 7.5 | 8
5 | 0.7 | 1.5 | 3 | 4.5 | 6 | 7.5 | 9 | 10.5 | 12 | 13.5 | 15 | 16.5
7.5 | 1.1 | 2.2 | 4.5 | 7 | 9 | 11 | 13.5 | 16 | 18 | 20 | 22.5 | 25
10 | 1.5 | 3 | 6 | 9 | 12 | 15 | 18 | 21 | 24 | 27 | 30 | 33
12.5 | 1.9 | 3.7 | 7 | 11 | 15 | 19 | 22.5 | 26 | 30 | 34 | 37.5 | 41
15 | 2.2 | 4.5 | 9 | 13.5 | 18 | 22.5 | 27 | 31.5 | 36 | 40.5 | 45 | 49.5

Concentrations of up to 5,000 mcg/mL have been administered to humans (250 mg/50 mL). The final volume administered should be determined by the fluid requirements of the patient.

Intravenous drug products should be inspected visually and should not be used if particulate matter or discoloration is present.

HOW SUPPLIED

Dobutamine Injection, USP is supplied in 20 mL single-dose glass vials containing 250 mg dobutamine, respectively, as the hydrochloride as follows:

Unit of Sale | Concentration
NDC 70436-203-80; Carton containing 1 Vial | 250 mg/20 mL; (12.5 mg/mL)
NDC 70436-203-82; Carton containing 10 Vials | 250 mg/20 mL; (12.5 mg/mL)

Store at 20° to 25°C (68° to 77°F). [See USP Controlled Room Temperature.]

Discard unused portion.

Manufactured by:

Hainan Poly Pharm. Co., Ltd.,

Guilinyang Economic Development Zone,

Haikou, Hainan, 571127, China

Distributed by:

Slate Run Pharmaceuticals, LLC.,

Columbus, Ohio 43215

10000396/01

Revised: 02/2023

Package/Label Display Panel

70436-203-80